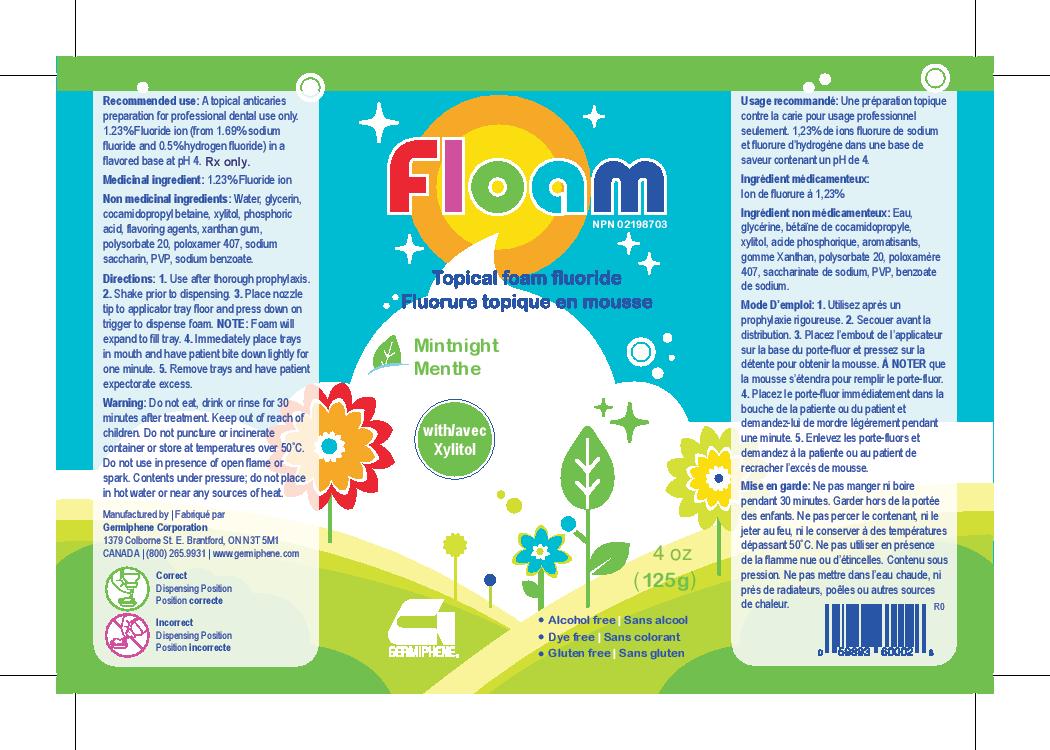 DRUG LABEL: Floam Topical Floam Fluoride
NDC: 61508-1120 | Form: AEROSOL, FOAM
Manufacturer: Germiphene Corporation
Category: otc | Type: HUMAN OTC DRUG LABEL
Date: 20170517

ACTIVE INGREDIENTS: SODIUM FLUORIDE 1.732 g/100 g
INACTIVE INGREDIENTS: HYDROFLUORIC ACID 1.039 g/100 g; GLYCERIN 14.96 g/100 g; POLYSORBATE 20 0.609 g/100 g; XANTHAN GUM 0.798 g/100 g; POLOXAMER 407 2.991 g/100 g; SODIUM BENZOATE 0.1 g/100 g; SACCHARIN SODIUM 0.199 g/100 g; XYLITOL 3.99 g/100 g; COCAMIDOPROPYL BETAINE 4.985 g/100 g; POVIDONE 0.1 g/100 g; SODIUM PHOSPHATE, DIBASIC 2.493 g/100 g; WATER 66.004 g/100 g

Recommended use:

A topical anticaries preparation for professional dental use only.

PURPOSE

1.23% fluoride ion (from 1.69% sodium fluoride and 0.5% hydrogen fluoride) in a flavored base at pH 4.

Medicinal ingredients:

1.23% fluoride ion.

Non-medicinal ingredients:

Water, glycerin, cocamidopropyl betaine, xylitol, phosphoric acid, flavouring agents, xanthan gum, polysorbate 20, poloxamer 407, sodium saccharin, PVP, sodium benzoate

Directions:

1. Use after thorough prophylaxis. 2. Shake prior to dispensing. 3. Place nozzle tip to applicator floor and press down on trigger to dispense foam. NOTE: Foam will expand to fill tray. 4. Immediately place trays in mouth and have patient bite down lightly for one minute. 5. Remove trays and have patient expectorate excess.

Warning:

Do not eat, drink, or rinse for 30 minutes after treatment. Do not puncture or incinerate container or store at temperatures over 50°C. Do not use in presence of open flame or spark. Contents under pressure; do not place in hot water or near any sources of heat.

Kep out of reach of children.